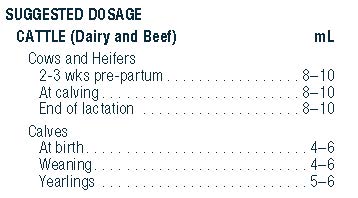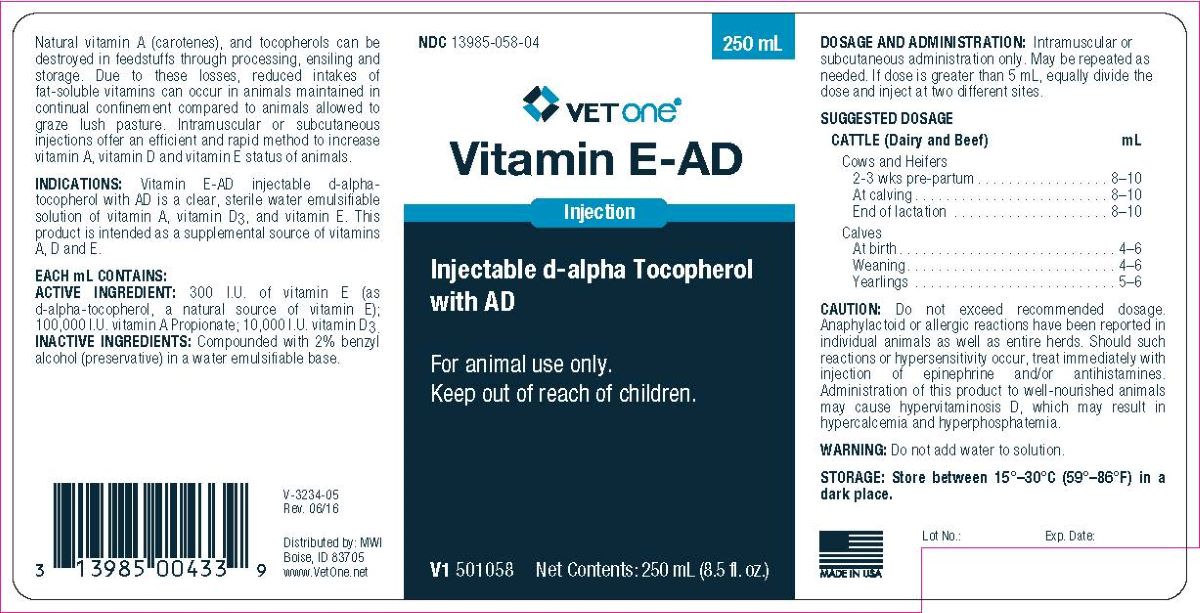 DRUG LABEL: Vitamin E-AD
NDC: 13985-058 | Form: INJECTION
Manufacturer: MWI/VetOne
Category: animal | Type: OTC ANIMAL DRUG LABEL
Date: 20231211

ACTIVE INGREDIENTS: .ALPHA.-TOCOPHEROL, D- 201 mg/1 mL; VITAMIN A 3.6 mg/1 mL; VITAMIN D 2.5 mg/1 mL

Vitamin E-AD

INDICATIONS AND USAGE

Vitamin E-AD

Injectable d-alphaTocopherol with AD

For animal use only.

Keep out of reach of children.

Natural vitamin A (carotenes), and tocopherols can be destroyed in feedstuffs through processing, ensiling and storage. Due to these losses, reduced intakes of fat-soluble vitamins can occur in animals maintained in continual confinement compared to animals allowed to graze in lush pasture. Intramuscular or subcutaneous injections offer an efficient and rapid method to increase vitamin A, vitamin D and Vitamin E status of animals.

Indications: Vitamin E-AD injectable d-alpha-tocopherol with AD is a clear, sterile sterile water emulsifiable solution of vitamin A,vitamin D3, and vitamin E. The product is intended as a supplemental source of vitamins A, D and E.

EACH mL CONTAINS:

ACTIVE INGREDIENTS: 300 I.U. vitamin E (as d-alpha-tocopherol, a natural source of vitamin E); 100,000 I.U. Vitamin A Propionate; 10,000 I.U. Vitamin D3.

INACTIVE INGREDIENTS: Compounded with 2% benzyl alcohol (preservative) in a water emulsifiable base.

CAUTION:

Do not exceed recommended dosage. Anaphylactoid or allergic reactions have been reported in individual animals as well as entire herds. Should such reactions or hypersensitivity occur, treat immediately with injection of epinephrine and/or antihistamines. Administration of this product to well-nourished animals may cause hypervitaminosis D, which may result in hypercalcemia and hyperphosphatemia.

WARNING:

Do not add water to solution.

STORAGE:

Store between 15°—30°C (59°—86°F) in a dark place.

ADMINISTRATION AND DOSAGE:

Intramuscular or Subcutaneous Administration Only. May be repeated. If dose is greater than 5 mL, equally divide the dose and inject at two different sites.